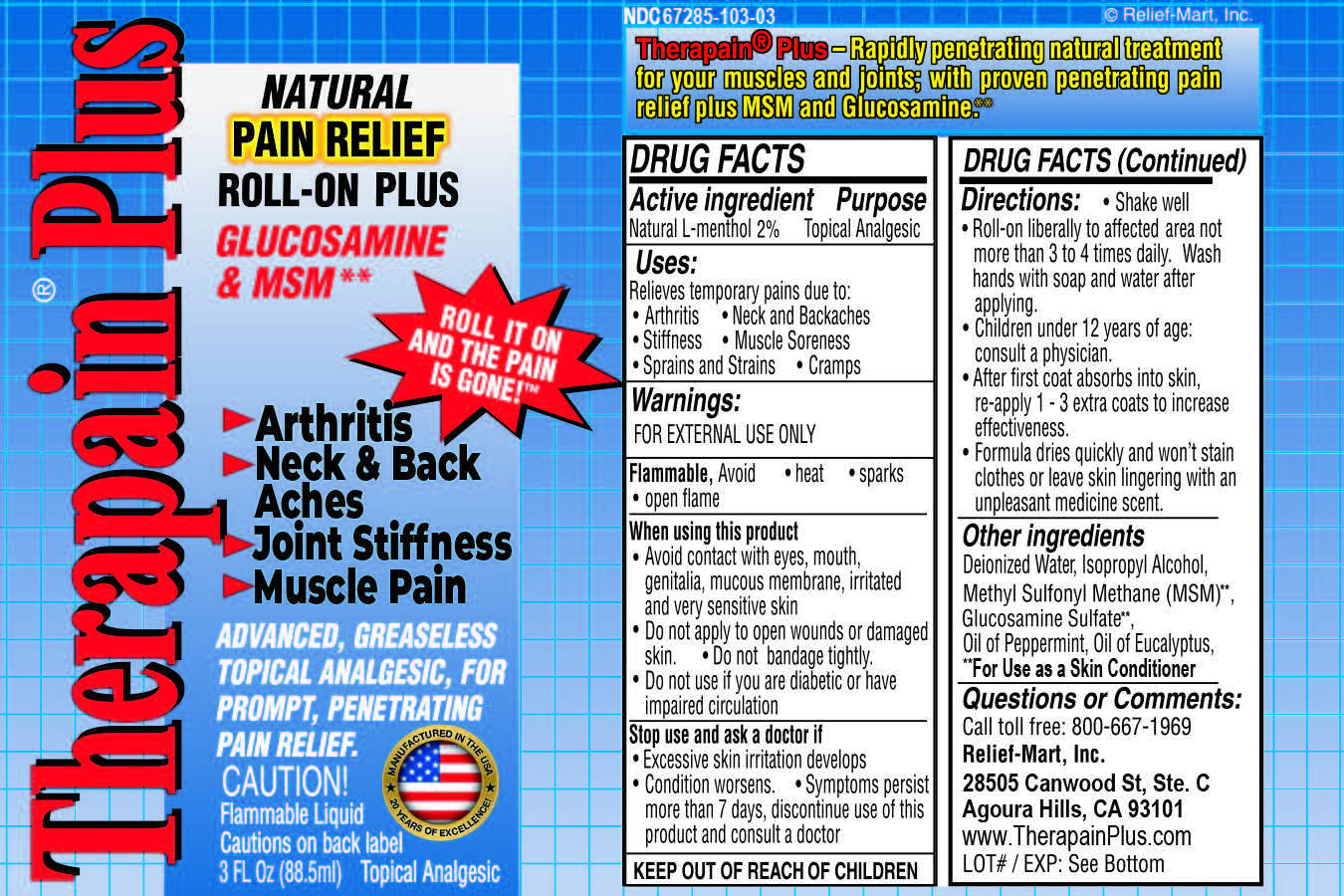 DRUG LABEL: Therapain Plus
NDC: 58418-827 | Form: LIQUID
Manufacturer: Epic Laboratories, LLC
Category: otc | Type: HUMAN OTC DRUG LABEL
Date: 20241231

ACTIVE INGREDIENTS: MENTHOL 2 g/100 mL
INACTIVE INGREDIENTS: EUCALYPTUS OIL; GLUCOSAMINE SULFATE; WATER; DIMETHYL SULFONE; PROPYLENE GLYCOL; PEPPERMINT OIL; ISOPROPYL ALCOHOL

Therapain Plus Roll On

Active Ingredient

Natural L-menthol 2%

Purpose

Topical Analgesic

Uses:

Relieves temporary pains due to:

- Arthritis
- Stiffness
- Sprains and Strains
- Neck and barckaches
- Muscle Soreness
- Cramps

Warnings:

FOR EXTERNAL USE ONLY

WARNINGS AND PRECAUTIONS

Flammable, Avoid

- heat
- sparks
- open flame

When using this product

- Avoid contact with eyes, mouth, genitalia, mucous membrane, irritated and very sensitive skin
- Do not apply to open wounds or damaged skin.
- Do not bandage tightly.
- Do not. use if you are diabetic or have impaired circulation

Stop use and ask a doctor if

- Excessive skin irritation develops
- Condition worsens.
- Symptoms persist more than 7 days, discontinue use of this product and consult a doctor

KEEP OUT OF REACH OF CHILDREN

Directions:

- Shake well
- Roll-on liberally to affected area not more than 3 to 4 times daily. Wash hands with soap and water after applying.
- Children under 12years of age: consult a physician.
- After first coat absorbs into skin, re-apply 1-3 extra coats to increase effectiveness.
- Formula dries quickly and won't stain clothes or leave skin lingering with an unplesant medicine scent.

INACTIVE INGREDIENT

Other ingredients

Deionized Water, Isopropyl Alcohol, Methyl Sulfonyl Methane (MSM)**,

Glucosamine Sulfate**, Oil of Peppermint, Oil of Eucalyptus,

**For Use as a Skin Conditioner

Questions or Comments:

Call toll free: 800-667-1969

Relief-Mart, Inc.

28505 Canwood St. Ste. C

Agoura Hills, CA 93101

www.TherapainPlus.com